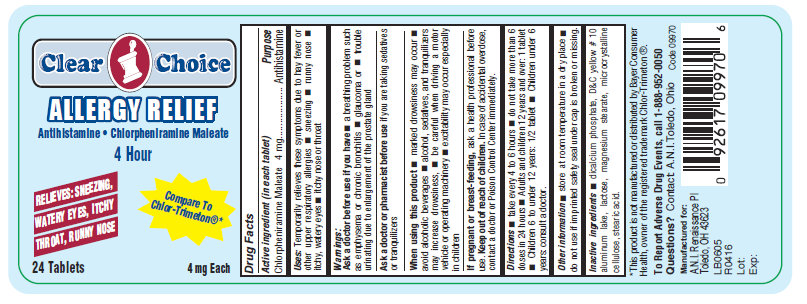 DRUG LABEL: Clear Choice Allergy Relief
NDC: 53185-001 | Form: TABLET
Manufacturer: Athlete's Needs Inc
Category: otc | Type: HUMAN OTC DRUG LABEL
Date: 20161107

ACTIVE INGREDIENTS: CHLORPHENIRAMINE MALEATE 4 mg/1 1
INACTIVE INGREDIENTS: D&C YELLOW NO. 10; LACTOSE; MAGNESIUM STEARATE; CELLULOSE, MICROCRYSTALLINE; STEARIC ACID

Clear Choice Allergy Relief

Drug Facts

Active ingredient (in each tablet)

Chlorpheniramine Maleate 4 mg

Purpose

Antihistamine

INDICATIONS AND USAGE

USES: Temporarily relieves these symptoms due to hay fever or other upper respiratory allergies, sneezing, runny nose, itchy, watery eyes, itchy nose or throat

Warnings:

Ask a doctor before use if you have

a breathing problem such as emphysema or chronic bronchitis

glaucoma or

trouble urinating due to enlargement of the prostate gland

Ask a doctor or pharmacist before use if you are taking sedatives or tranquilizers

When using this product

marked drowsiness may occur

avoid alcoholic beverages

alcohol, sedatives, and tranquilizers may increase drowsiness

be careful when driving a motor vehicle or operating machinery

excitability may occur especially in children

PREGNANCY OR BREAST FEEDING

If pregnant or breast-feeding, ask a health professional before use.

Keep out of reach of children. In case of accidental overdose, contact a doctor or Poison Control Center immediately

Directions

- take every 4 to 6 hours,
- do not take more than 6 does in 24 hours
- Adults and children 12 years and over: 1 tablet
- Children 6 to under 12 years: 1/2 tablet
- Children under 6 years: consult a doctor

Other Information

store at room temperature in a dry place

do not use if imprinted safety seal under cap is broken or missing.

INACTIVE INGREDIENT

Inactive Ingredients: dicalcium phosphate, D&C yellow # 10 aluminum lake, lactose, magnesium stearate, microcrystalline
cellulose, stearic acid.

This product is not manufactured or distributed by Schering-Plough, owner of the registered trademark Chlor-Trimeton(R).

QUESTIONS

To Report Adverse Drug Events, call 1-888-952-0050

Questions? Contact A.N.I. Toledo, Ohio

Manufactured for:

A.N.I. Toledo, OH 43623

PACKAGE LABEL

Clear Choice

ALLERGY RELIEF

Antihistamine Chlorpheniramine Maleate

4 Hour

RELIEVES: SNEEZING, WATERY EYES, ITCHY THROAT, RUNNY NOSE

Compare to Chlor-Trimeton(R)

24 Tablets

4 mg Each